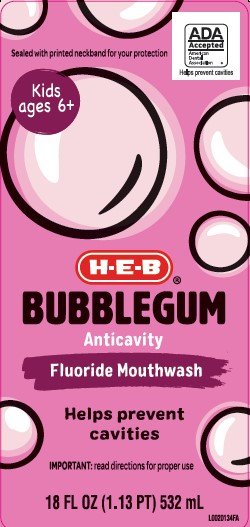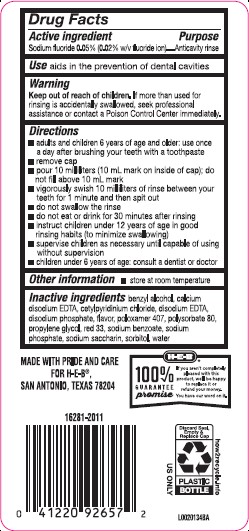 DRUG LABEL: Anticavity Rinse
NDC: 37808-808 | Form: MOUTHWASH
Manufacturer: H E B
Category: otc | Type: HUMAN OTC DRUG LABEL
Date: 20260224

ACTIVE INGREDIENTS: SODIUM FLUORIDE 0.2 mg/1 mL
INACTIVE INGREDIENTS: BENZYL ALCOHOL; EDETATE CALCIUM DISODIUM ANHYDROUS; CETYLPYRIDINIUM CHLORIDE; EDETATE DISODIUM; SODIUM PHOSPHATE, DIBASIC, ANHYDROUS; POLOXAMER 407; POLYSORBATE 80; PROPYLENE GLYCOL; D&C RED NO. 33; SODIUM BENZOATE; SODIUM PHOSPHATE; SACCHARIN SODIUM; SORBITOL; WATER

HEB 004.002/004AE
Anticavity Fluoride Rinse, Bubble Gum

Active ingredient

Sodium Fluoride 0.05% (0.02% w/v fluoride ion)

Purpose

Anticavity Rinse

Use

aids in the prevention of dental cavities

Warnings

for this product

Keep out of reach of children.

If more than used for rinsing is accidentally swallowed, seek professional assistance or contact a Poison Control Center immediately.

Directions

- adults and children 6 year of age and older: use once a day after brushing your teeth with a toothpaste
- remove cap
- pour 10 milliliters (10 mL mark on inside of cap), do not fill above 10 mL mark
- vigorously swish 10 milliliters of rinse between your teeth for 1 minute and then spit out
- do not swallow the rinse
- do not eat or drink for 30 minutes after rinsing
- instruct children under 12 years of age in good rinsing habits (to minimize swallowing)
- supervise children as necessary until capable of using without supervision
- children under 6 year of age: consult a dentist or doctor

Other information

- store at room temperature

Inactive ingredients

benzyl alcohol, calcium disodium EDTA, cetylpyridinium chloride, disodium EDTA, disodium phosphate, flavor, poloxomer 407, polysorbate 80, propylene glycol, red 33, sodium benzoate, sodium phosphate, sodium saccharin, sorbitol, water

ADVERSE REACTION

MADE WITH PRIDE AND CARE FOR H-E-B®,

San Antonio, TX 78204

100% GUARANTEE promise

If you aren't completely pleased with this product, we'll be happy to replace it or refund your money.

You have our word on it.

US ONLY

Discard Seal, Empty & Replace Cap

PLASTIC BOTTLE

how2recycle.com

Principal display panel

ADA Accepted

American Dental Association

Helps prevent cavities

Sealed with printed neckband for your protection

Kids ages 6+

H-E-B®

BUBBLEGUM

Anticavity

Fluoride Mouthwash

Helps prevent cavities

IMPORTANT: read directions for proper use

18 FL OZ (1.13 PT) 532 mL